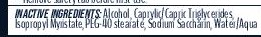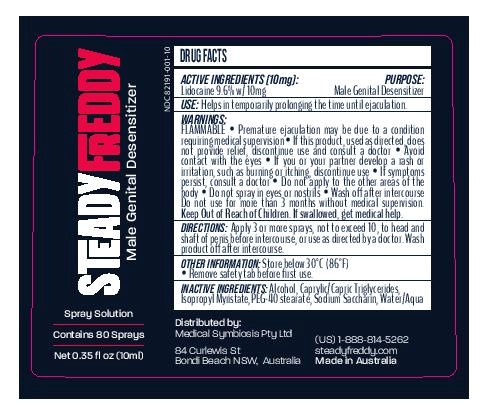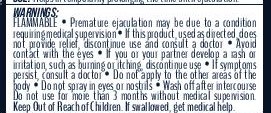 DRUG LABEL: Steady Freddy
NDC: 82191-001 | Form: SPRAY
Manufacturer: Medical Symbiosis Pty Ltd
Category: otc | Type: HUMAN OTC DRUG LABEL
Date: 20251231

ACTIVE INGREDIENTS: LIDOCAINE 96 mg/1 mL
INACTIVE INGREDIENTS: WATER; PEG-40 STEARATE; SACCHARIN SODIUM; ALCOHOL; ISOPROPYL MYRISTATE; MEDIUM-CHAIN TRIGLYCERIDES

Steady Freddy 10 ml spray

Purpose

Topical Anesthetic- Male Genital Desensitizer

Directions

Directions: Apply 3 or more sprays, not to exceed 10, to head and shaft of penis before intercourse, or use as directed by a doctor. Wash product off after intercourse.

Active Ingredient

Lidocaine 9.6% w/ 10mg (Per Spray)

Keep Out of Reach of Children. If swallowed, get medical help.

Uses

Helps in temporarily prolonging the time until ejaculation.